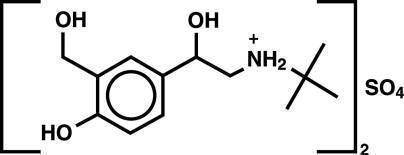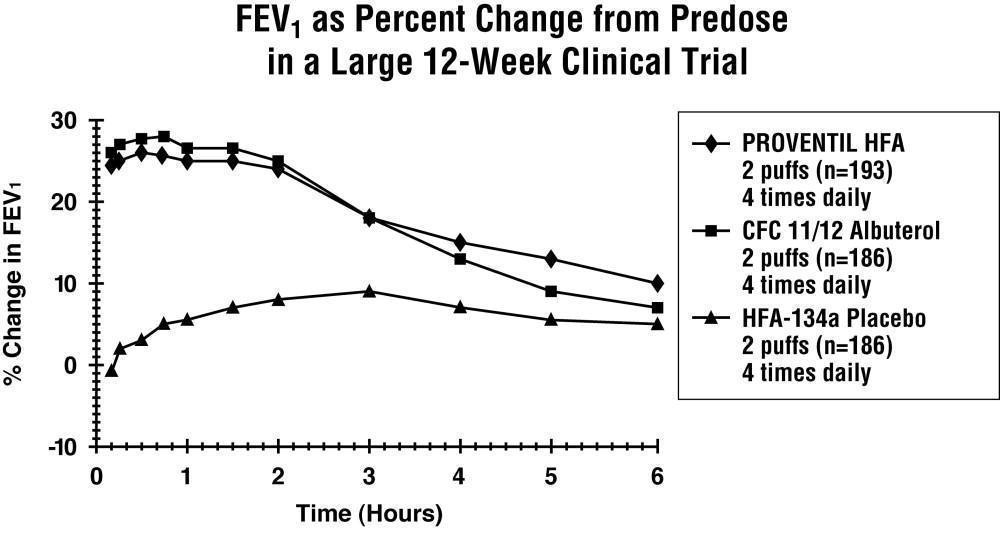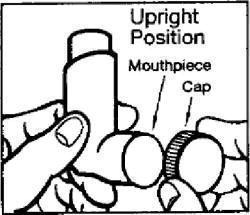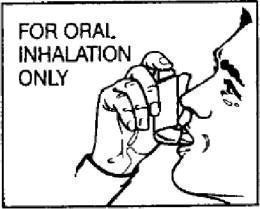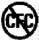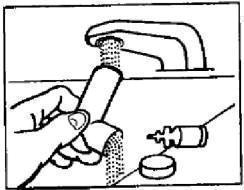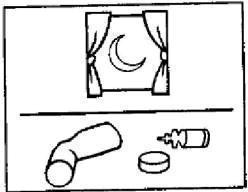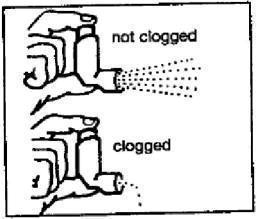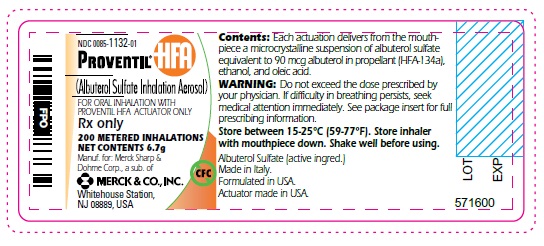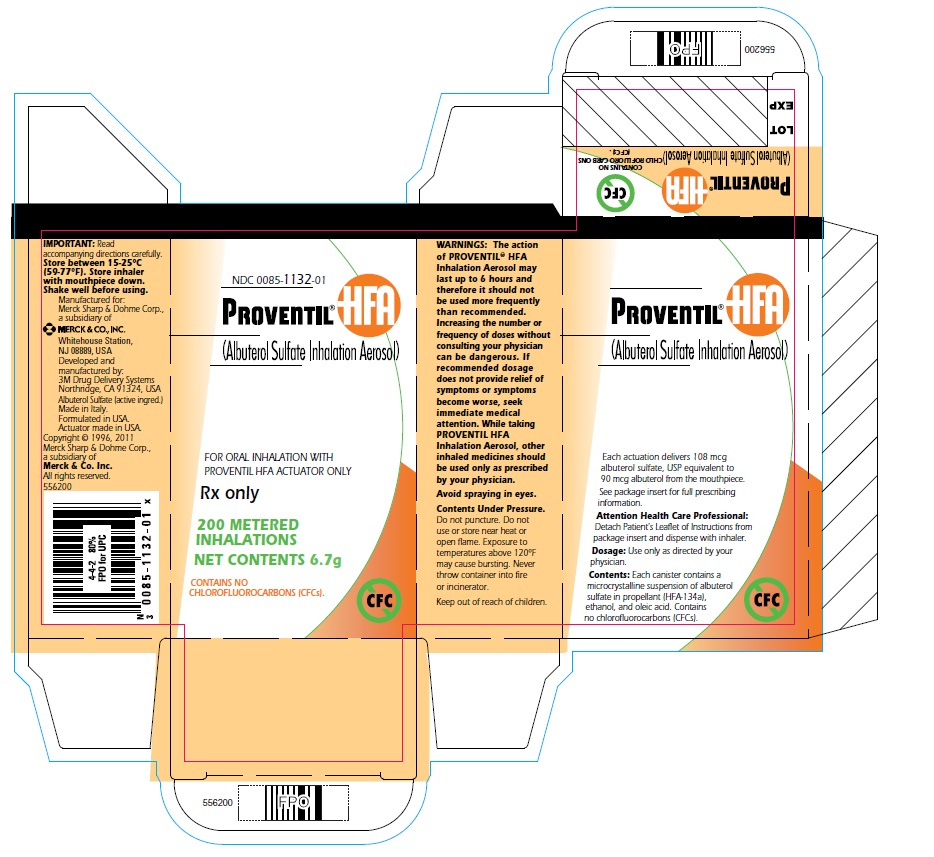 DRUG LABEL: Proventil HFA
NDC: 0085-1132 | Form: AEROSOL, METERED
Manufacturer: Merck Sharp & Dohme Corp.
Category: prescription | Type: HUMAN PRESCRIPTION DRUG LABEL
Date: 20191007

ACTIVE INGREDIENTS: Albuterol Sulfate 108 ug/1 1
INACTIVE INGREDIENTS: alcohol; NORFLURANE; Oleic acid

PROVENTIL® HFA
(albuterol sulfate)
Inhalation Aerosol

FOR ORAL INHALATION ONLY

Prescribing Information

DESCRIPTION

The active component of PROVENTIL® HFA (albuterol sulfate) Inhalation Aerosol is albuterol sulfate, USP racemic α^1 [(tert-Butylamino)methyl]-4-hydroxy-m-xylene-α,α'-diol sulfate (2:1)(salt), a relatively selective beta2-adrenergic bronchodilator having the following chemical structure:

Albuterol sulfate is the official generic name in the United States. The World Health Organization recommended name for the drug is salbutamol sulfate. The molecular weight of albuterol sulfate is 576.7, and the empirical formula is (C13H21 NO3)2•H2SO4. Albuterol sulfate is a white to off-white crystalline solid. It is soluble in water and slightly soluble in ethanol. PROVENTIL HFA Inhalation Aerosol is a pressurized metered-dose aerosol unit for oral inhalation. It contains a microcrystalline suspension of albuterol sulfate in propellant HFA-134a (1,1,1,2-tetrafluoroethane), ethanol, and oleic acid.

Each actuation delivers 120 mcg albuterol sulfate, USP from the valve and 108 mcg albuterol sulfate, USP from the mouthpiece (equivalent to 90 mcg of albuterol base from the mouthpiece). Each canister provides 200 inhalations. It is recommended to prime the inhaler before using for the first time and in cases where the inhaler has not been used for more than 2 weeks by releasing four “test sprays” into the air, away from the face.

This product does not contain chlorofluorocarbons (CFCs) as the propellant.

CLINICAL PHARMACOLOGY

Mechanism of Action In vitro studies and in vivo pharmacologic studies have demonstrated that albuterol has a preferential effect on beta2-adrenergic receptors compared with isoproterenol. While it is recognized that beta2-adrenergic receptors are the predominant receptors on bronchial smooth muscle, data indicate that there is a population of beta2-receptors in the human heart existing in a concentration between 10% and 50% of cardiac beta-adrenergic receptors. The precise function of these receptors has not been established. (See WARNINGS, Cardiovascular Effects section.)

Activation of beta2-adrenergic receptors on airway smooth muscle leads to the activation of adenylcyclase and to an increase in the intracellular concentration of cyclic-3',5'-adenosine monophosphate (cyclic AMP). This increase of cyclic AMP leads to the activation of protein kinase A, which inhibits the phosphorylation of myosin and lowers intracellular ionic calcium concentrations, resulting in relaxation. Albuterol relaxes the smooth muscles of all airways, from the trachea to the terminal bronchioles. Albuterol acts as a functional antagonist to relax the airway irrespective of the spasmogen involved, thus protecting against all bronchoconstrictor challenges. Increased cyclic AMP concentrations are also associated with the inhibition of release of mediators from mast cells in the airway.

Albuterol has been shown in most clinical trials to have more effect on the respiratory tract, in the form of bronchial smooth muscle relaxation, than isoproterenol at comparable doses while producing fewer cardiovascular effects. Controlled clinical studies and other clinical experience have shown that inhaled albuterol, like other beta-adrenergic agonist drugs, can produce a significant cardiovascular effect in some patients, as measured by pulse rate, blood pressure, symptoms, and/or electrocardiographic changes.

Preclinical Intravenous studies in rats with albuterol sulfate have demonstrated that albuterol crosses the blood-brain barrier and reaches brain concentrations amounting to approximately 5% of the plasma concentrations. In structures outside the blood-brain barrier (pineal and pituitary glands), albuterol concentrations were found to be 100 times those in the whole brain.

Studies in laboratory animals (minipigs, rodents, and dogs) have demonstrated the occurrence of cardiac arrhythmias and sudden death (with histologic evidence of myocardial necrosis) when beta2-agonist and methylxanthines were administered concurrently. The clinical significance of these findings is unknown.

Propellant HFA-134a is devoid of pharmacological activity except at very high doses in animals (380-1300 times the maximum human exposure based on comparisons of AUC values), primarily producing ataxia, tremors, dyspnea, or salivation. These are similar to effects produced by the structurally related chlorofluorocarbons (CFCs), which have been used extensively in metered dose inhalers.

In animals and humans, propellant HFA-134a was found to be rapidly absorbed and rapidly eliminated, with an elimination half-life of 3 to 27 minutes in animals and 5 to 7 minutes in humans. Time to maximum plasma concentration (Tmax) and mean residence time are both extremely short, leading to a transient appearance of HFA-134a in the blood with no evidence of accumulation.

PHARMACOKINETICS

Pharmacokinetics In a single-dose bioavailability study which enrolled six healthy, male volunteers, transient low albuterol levels (close to the lower limit of quantitation) were observed after administration of two puffs from both PROVENTIL® HFA Inhalation Aerosol and a CFC 11/12 propelled albuterol inhaler. No formal pharmacokinetic analyses were possible for either treatment, but systemic albuterol levels appeared similar.

Clinical Trials In a 12-week, randomized, double-blind, double-dummy, active- and placebo-controlled trial, 565 patients with asthma were evaluated for the bronchodilator efficacy of PROVENTIL HFA Inhalation Aerosol (193 patients) in comparison to a CFC 11/12 propelled albuterol inhaler (186 patients) and an HFA-134a placebo inhaler (186 patients).

Serial FEV1 measurements (shown below as percent change from test-day baseline) demonstrated that two inhalations of PROVENTIL HFA Inhalation Aerosol produced significantly greater improvement in pulmonary function than placebo and produced outcomes which were clinically comparable to a CFC 11/12 propelled albuterol inhaler.

The mean time to onset of a 15% increase in FEV1 was 6 minutes and the mean time to peak effect was 50 to 55 minutes. The mean duration of effect as measured by a 15% increase in FEV1 was 3 hours. In some patients, duration of effect was as long as 6 hours.

In another clinical study in adults, two inhalations of PROVENTIL HFA Inhalation Aerosol taken 30 minutes before exercise prevented exercise-induced bronchospasm as demonstrated by the maintenance of FEV1 within 80% of baseline values in the majority of patients.

In a 4-week, randomized, open-label trial, 63 children, 4 to 11 years of age, with asthma were evaluated for the bronchodilator efficacy of PROVENTIL HFA Inhalation Aerosol (33 pediatric patients) in comparison to a CFC 11/12 propelled albuterol inhaler (30 pediatric patients).

Serial FEV1 measurements as percent change from test-day baseline demonstrated that two inhalations of PROVENTIL HFA Inhalation Aerosol produced outcomes which were clinically comparable to a CFC 11/12 propelled albuterol inhaler.

The mean time to onset of a 12% increase in FEV1 for PROVENTIL HFA Inhalation Aerosol was 7 minutes and the mean time to peak effect was approximately 50 minutes. The mean duration of effect as measured by a 12% increase in FEV1 was 2.3 hours. In some pediatric patients, duration of effect was as long as 6 hours.

In another clinical study in pediatric patients, two inhalations of PROVENTIL HFA Inhalation Aerosol taken 30 minutes before exercise provided comparable protection against exercise-induced bronchospasm as a CFC 11/12 propelled albuterol inhaler.

INDICATIONS AND USAGE

PROVENTIL® HFA Inhalation Aerosol is indicated in adults and children 4 years of age and older for the treatment or prevention of bronchospasm with reversible obstructive airway disease and for the prevention of exercise-induced bronchospasm.

CONTRAINDICATIONS

PROVENTIL® HFA Inhalation Aerosol is contraindicated in patients with a history of hypersensitivity to albuterol or any other PROVENTIL HFA components.

WARNINGS

1. Paradoxical Bronchospasm: Inhaled albuterol sulfate can produce paradoxical bronchospasm that may be life threatening. If paradoxical bronchospasm occurs, PROVENTIL® HFA Inhalation Aerosol should be discontinued immediately and alternative therapy instituted. It should be recognized that paradoxical bronchospasm, when associated with inhaled formulations, frequently occurs with the first use of a new canister.
2. Deterioration of Asthma: Asthma may deteriorate acutely over a period of hours or chronically over several days or longer. If the patient needs more doses of PROVENTIL HFA Inhalation Aerosol than usual, this may be a marker of destabilization of asthma and requires re-evaluation of the patient and treatment regimen, giving special consideration to the possible need for anti-inflammatory treatment, e.g., corticosteroids.
3. Use of Anti-inflammatory Agents: The use of beta-adrenergic-agonist bronchodilators alone may not be adequate to control asthma in many patients. Early consideration should be given to adding anti-inflammatory agents, e.g., corticosteroids, to the therapeutic regimen.
4. Cardiovascular Effects: PROVENTIL HFA Inhalation Aerosol, like other beta-adrenergic agonists, can produce clinically significant cardiovascular effects in some patients as measured by pulse rate, blood pressure, and/or symptoms. Although such effects are uncommon after administration of PROVENTIL HFA Inhalation Aerosol at recommended doses, if they occur, the drug may need to be discontinued. In addition, beta-agonists have been reported to produce ECG changes, such as flattening of the T wave, prolongation of the QTc interval, and ST segment depression. The clinical significance of these findings is unknown. Therefore, PROVENTIL HFA Inhalation Aerosol, like all sympathomimetic amines, should be used with caution in patients with cardiovascular disorders, especially coronary insufficiency, cardiac arrhythmias, and hypertension.
5. Do Not Exceed Recommended Dose: Fatalities have been reported in association with excessive use of inhaled sympathomimetic drugs in patients with asthma. The exact cause of death is unknown, but cardiac arrest following an unexpected development of a severe acute asthmatic crisis and subsequent hypoxia is suspected.
6. Immediate Hypersensitivity Reactions: Immediate hypersensitivity reactions may occur after administration of albuterol sulfate, as demonstrated by rare cases of urticaria, angioedema, rash, bronchospasm, anaphylaxis, and oropharyngeal edema.

PRECAUTIONS

GENERAL PRECAUTIONS

General Albuterol sulfate, as with all sympathomimetic amines, should be used with caution in patients with cardiovascular disorders, especially coronary insufficiency, cardiac arrhythmias, and hypertension; in patients with convulsive disorders, hyperthyroidism, or diabetes mellitus; and in patients who are unusually responsive to sympathomimetic amines. Clinically significant changes in systolic and diastolic blood pressure have been seen in individual patients and could be expected to occur in some patients after use of any beta-adrenergic bronchodilator.

Large doses of intravenous albuterol have been reported to aggravate preexisting diabetes mellitus and ketoacidosis. As with other beta-agonists, albuterol may produce significant hypokalemia in some patients, possibly through intracellular shunting, which has the potential to produce adverse cardiovascular effects. The decrease is usually transient, not requiring supplementation.

PATIENT COUNSELING INFORMATION

Information for Patients See illustrated Patient's Instructions for Use. SHAKE WELL BEFORE USING. Patients should be given the following information:

It is recommended to prime the inhaler before using for the first time and in cases where the inhaler has not been used for more than 2 weeks by releasing four “test sprays” into the air, away from the face.

KEEPING THE PLASTIC MOUTHPIECE CLEAN IS VERY IMPORTANT TO PREVENT MEDICATION BUILDUP AND BLOCKAGE. THE MOUTHPIECE SHOULD BE WASHED, SHAKEN TO REMOVE EXCESS WATER, AND AIR DRIED THOROUGHLY AT LEAST ONCE A WEEK. INHALER MAY CEASE TO DELIVER MEDICATION IF NOT PROPERLY CLEANED.

The mouthpiece should be cleaned (with the canister removed) by running warm water through the top and bottom for 30 seconds at least once a week. The mouthpiece must be shaken to remove excess water, then air dried thoroughly (such as overnight). Blockage from medication buildup or improper medication delivery may result from failure to thoroughly air dry the mouthpiece.

If the mouthpiece should become blocked (little or no medication coming out of the mouthpiece), the blockage may be removed by washing as described above.

If it is necessary to use the inhaler before it is completely dry, shake off excess water, replace canister, test spray twice away from face, and take the prescribed dose. After such use, the mouthpiece should be rewashed and allowed to air dry thoroughly.

The action of PROVENTIL® HFA Inhalation Aerosol should last up to 4 to 6 hours. PROVENTIL HFA Inhalation Aerosol should not be used more frequently than recommended. Do not increase the dose or frequency of doses of PROVENTIL HFA Inhalation Aerosol without consulting your physician. If you find that treatment with PROVENTIL HFA Inhalation Aerosol becomes less effective for symptomatic relief, your symptoms become worse, and/or you need to use the product more frequently than usual, medical attention should be sought immediately. While you are taking PROVENTIL HFA Inhalation Aerosol, other inhaled drugs and asthma medications should be taken only as directed by your physician.

Common adverse effects of treatment with inhaled albuterol include palpitations, chest pain, rapid heart rate, tremor, or nervousness. If you are pregnant or nursing, contact your physician about use of PROVENTIL HFA Inhalation Aerosol. Effective and safe use of PROVENTIL HFA Inhalation Aerosol includes an understanding of the way that it should be administered. Use PROVENTIL HFA Inhalation Aerosol only with the actuator supplied with the product. Discard the canister after 200 sprays have been used.

In general, the technique for administering PROVENTIL HFA Inhalation Aerosol to children is similar to that for adults. Children should use PROVENTIL HFA Inhalation Aerosol under adult supervision, as instructed by the patient's physician. (See Patient's Instructions for Use.)

Drug Interactions

1. Beta-Blockers: Beta-adrenergic-receptor blocking agents not only block the pulmonary effect of beta-agonists, such as PROVENTIL HFA Inhalation Aerosol, but may produce severe bronchospasm in asthmatic patients. Therefore, patients with asthma should not normally be treated with beta-blockers. However, under certain circumstances, e.g., as prophylaxis after myocardial infarction, there may be no acceptable alternatives to the use of beta-adrenergic blocking agents in patients with asthma. In this setting, cardioselective beta-blockers should be considered, although they should be administered with caution.
2. Diuretics: The ECG changes and/or hypokalemia which may result from the administration of nonpotassium-sparing diuretics (such as loop or thiazide diuretics) can be acutely worsened by beta-agonists, especially when the recommended dose of the beta-agonist is exceeded. Although the clinical significance of these effects is not known, caution is advised in the coadministration of beta-agonists with nonpotassium-sparing diuretics.
3. Albuterol-Digoxin: Mean decreases of 16% and 22% in serum digoxin levels were demonstrated after single-dose intravenous and oral administration of albuterol, respectively, to normal volunteers who had received digoxin for 10 days. The clinical significance of these findings for patients with obstructive airway disease who are receiving albuterol and digoxin on a chronic basis is unclear; nevertheless, it would be prudent to carefully evaluate the serum digoxin levels in patients who are currently receiving digoxin and albuterol.
4. Monoamine Oxidase Inhibitors or Tricyclic Antidepressants: PROVENTIL HFA Inhalation Aerosol should be administered with extreme caution to patients being treated with monoamine oxidase inhibitors or tricyclic antidepressants, or within 2 weeks of discontinuation of such agents, because the action of albuterol on the cardiovascular system may be potentiated.

Carcinogenesis, Mutagenesis, and Impairment of Fertility

In a 2-year study in SPRAGUE-DAWLEY® rats, albuterol sulfate caused a dose-related increase in the incidence of benign leiomyomas of the mesovarium at the above dietary doses of 2 mg/kg (approximately 15 times the maximum recommended daily inhalation dose for adults on a mg/m^2 basis and approximately 6 times the maximum recommended daily inhalation dose for children on a mg/m^2 basis). In another study this effect was blocked by the coadministration of propranolol, a nonselective beta-adrenergic antagonist. In an 18-month study in CD-1 mice, albuterol sulfate showed no evidence of tumorigenicity at dietary doses of up to 500 mg/kg (approximately 1700 times the maximum recommended daily inhalation dose for adults on a mg/m^2 basis and approximately 800 times the maximum recommended daily inhalation dose for children on a mg/m^2 basis). In a 22-month study in Golden Hamsters, albuterol sulfate showed no evidence of tumorigenicity at dietary doses of up to 50 mg/kg (approximately 225 times the maximum recommended daily inhalation dose for adults on a mg/m^2 basis and approximately 110 times the maximum recommended daily inhalation dose for children on a mg/m^2 basis).

Albuterol sulfate was not mutagenic in the Ames test or a mutation test in yeast. Albuterol sulfate was not clastogenic in a human peripheral lymphocyte assay or in an AH1 strain mouse micronucleus assay.

Reproduction studies in rats demonstrated no evidence of impaired fertility at oral doses up to 50 mg/kg (approximately 340 times the maximum recommended daily inhalation dose for adults on a mg/m^2 basis).

Pregnancy Teratogenic Effects

Albuterol sulfate has been shown to be teratogenic in mice. A study in CD-1 mice given albuterol sulfate subcutaneously showed cleft palate formation in 5 of 111 (4.5%) fetuses at 0.25 mg/kg (less than the maximum recommended daily inhalation dose for adults on a mg/m^2 basis) and in 10 of 108 (9.3%) fetuses at 2.5 mg/kg (approximately 8 times the maximum recommended daily inhalation dose for adults on a mg/m^2 basis). The drug did not induce cleft palate formation at a dose of 0.025 mg/kg (less than the maximum recommended daily inhalation dose for adults on a mg/m^2 basis). Cleft palate also occurred in 22 of 72 (30.5%) fetuses from females treated subcutaneously with 2.5 mg/kg of isoproterenol (positive control).

A reproduction study in Stride Dutch rabbits revealed cranioschisis in 7 of 19 (37%) fetuses when albuterol sulfate was administered orally at 50 mg/kg dose (approximately 680 times the maximum recommended daily inhalation dose for adults on a mg/m^2 basis).

In an inhalation reproduction study in SPRAGUE-DAWLEY rats, the albuterol sulfate/HFA-134a formulation did not exhibit any teratogenic effects at 10.5 mg/kg (approximately 70 times the maximum recommended daily inhalation dose for adults on a mg/m^2 basis).

A study in which pregnant rats were dosed with radiolabeled albuterol sulfate demonstrated that drug-related material is transferred from the maternal circulation to the fetus.

There are no adequate and well-controlled studies of PROVENTIL HFA Inhalation Aerosol or albuterol sulfate in pregnant women. PROVENTIL HFA Inhalation Aerosol should be used during pregnancy only if the potential benefit justifies the potential risk to the fetus.

During worldwide marketing experience, various congenital anomalies, including cleft palate and limb defects, have been reported in the offspring of patients being treated with albuterol. Some of the mothers were taking multiple medications during their pregnancies. Because no consistent pattern of defects can be discerned, a relationship between albuterol use and congenital anomalies has not been established.

Use in Labor and Delivery

Because of the potential for beta-agonist interference with uterine contractility, use of PROVENTIL HFA Inhalation Aerosol for relief of bronchospasm during labor should be restricted to those patients in whom the benefits clearly outweigh the risk.

Tocolysis: Albuterol has not been approved for the management of preterm labor. The benefit:risk ratio when albuterol is administered for tocolysis has not been established. Serious adverse reactions, including pulmonary edema, have been reported during or following treatment of premature labor with beta2-agonists, including albuterol.

Nursing Mothers

Plasma levels of albuterol sulfate and HFA-134a after inhaled therapeutic doses are very low in humans, but it is not known whether the components of PROVENTIL HFA Inhalation Aerosol are excreted in human milk.

Because of the potential for tumorigenicity shown for albuterol in animal studies and lack of experience with the use of PROVENTIL HFA Inhalation Aerosol by nursing mothers, a decision should be made whether to discontinue nursing or to discontinue the drug, taking into account the importance of the drug to the mother. Caution should be exercised when albuterol sulfate is administered to a nursing woman.

Pediatrics

The safety and effectiveness of PROVENTIL HFA Inhalation Aerosol in pediatric patients below the age of 4 years have not been established.

Geriatrics

PROVENTIL HFA Inhalation Aerosol has not been studied in a geriatric population. As with other beta2-agonists, special caution should be observed when using PROVENTIL HFA Inhalation Aerosol in elderly patients who have concomitant cardiovascular disease that could be adversely affected by this class of drug.

ADVERSE REACTIONS

Adverse reaction information concerning PROVENTIL® HFA Inhalation Aerosol is derived from a 12-week, double-blind, double-dummy study which compared PROVENTIL HFA Inhalation Aerosol, a CFC 11/12 propelled albuterol inhaler, and an HFA-134a placebo inhaler in 565 asthmatic patients. The following table lists the incidence of all adverse events (whether considered by the investigator drug related or unrelated to drug) from this study which occurred at a rate of 3% or greater in the PROVENTIL HFA Inhalation Aerosol treatment group and more frequently in the PROVENTIL HFA Inhalation Aerosol treatment group than in the placebo group. Overall, the incidence and nature of the adverse reactions reported for PROVENTIL HFA Inhalation Aerosol and a CFC 11/12 propelled albuterol inhaler were comparable.

Adverse Experience Incidences (% of patients) in a Large 12-week Clinical Trial*
Body System/ Adverse Event (Preferred Term) |  | PROVENTIL® HFA Inhalation Aerosol (N=193) | CFC 11/12 Propelled Albuterol Inhaler (N=186) | HFA-134a Placebo Inhaler (N=186)
Application Site Disorders | Inhalation Site Sensation | 6 | 9 | 2
 | Inhalation Taste Sensation | 4 | 3 | 3
Body as a Whole | Allergic Reaction/Symptoms | 6 | 4 | <1
 | Back Pain | 4 | 2 | 3
 | Fever | 6 | 2 | 5
Central and Peripheral Nervous System | Tremor | 7 | 8 | 2
Gastrointestinal System | Nausea | 10 | 9 | 5
 | Vomiting | 7 | 2 | 3
Heart Rate and Rhythm Disorder | Tachycardia | 7 | 2 | <1
Psychiatric Disorders | Nervousness | 7 | 9 | 3
Respiratory System Disorders | Respiratory Disorder
 | (unspecified) | 6 | 4 | 5
 | Rhinitis | 16 | 22 | 14
 | Upper Resp Tract Infection | 21 | 20 | 18
Urinary System Disorder | Urinary Tract Infection | 3 | 4 | 2
*This table includes all adverse events (whether considered by the investigator drug related or unrelated to drug) which occurred at an incidence rate of at least 3.0% in the PROVENTIL HFA Inhalation Aerosol group and more frequently in the PROVENTIL HFA Inhalation Aerosol group than in the HFA-134a placebo inhaler group.

Adverse events reported by less than 3% of the patients receiving PROVENTIL HFA Inhalation Aerosol, and by a greater proportion of PROVENTIL HFA Inhalation Aerosol patients than placebo patients, which have the potential to be related to PROVENTIL HFA Inhalation Aerosol include: dysphonia, increased sweating, dry mouth, chest pain, edema, rigors, ataxia, leg cramps, hyperkinesia, eructation, flatulence, tinnitus, diabetes mellitus, anxiety, depression, somnolence, rash. Palpitation and dizziness have also been observed with PROVENTIL HFA Inhalation Aerosol.

Adverse events reported in a 4-week pediatric clinical trial comparing PROVENTIL HFA Inhalation Aerosol and a CFC 11/12 propelled albuterol inhaler occurred at a low incidence rate and were similar to those seen in the adult trials.

In small, cumulative dose studies, tremor, nervousness, and headache appeared to be dose related.

Rare cases of urticaria, angioedema, rash, bronchospasm, and oropharyngeal edema have been reported after the use of inhaled albuterol. In addition, albuterol, like other sympathomimetic agents, can cause adverse reactions such as hypertension, angina, vertigo, central nervous system stimulation, insomnia, headache, metabolic acidosis, and drying or irritation of the oropharynx.

OVERDOSAGE

The expected symptoms with overdosage are those of excessive beta-adrenergic stimulation and/or occurrence or exaggeration of any of the symptoms listed under ADVERSE REACTIONS, e.g., seizures, angina, hypertension or hypotension, tachycardia with rates up to 200 beats per minute, arrhythmias, nervousness, headache, tremor, dry mouth, palpitation, nausea, dizziness, fatigue, malaise, and insomnia.

Hypokalemia may also occur. As with all sympathomimetic medications, cardiac arrest and even death may be associated with abuse of PROVENTIL® HFA Inhalation Aerosol. Treatment consists of discontinuation of PROVENTIL HFA Inhalation Aerosol together with appropriate symptomatic therapy. The judicious use of a cardioselective beta-receptor blocker may be considered, bearing in mind that such medication can produce bronchospasm. There is insufficient evidence to determine if dialysis is beneficial for overdosage of PROVENTIL HFA Inhalation Aerosol.

The oral median lethal dose of albuterol sulfate in mice is greater than 2000 mg/kg (approximately 6800 times the maximum recommended daily inhalation dose for adults on a mg/m^2 basis and approximately 3200 times the maximum recommended daily inhalation dose for children on a mg/m^2 basis). In mature rats, the subcutaneous median lethal dose of albuterol sulfate is approximately 450 mg/kg (approximately 3000 times the maximum recommended daily inhalation dose for adults on a mg/m^2 basis and approximately 1400 times the maximum recommended daily inhalation dose for children on a mg/m^2 basis). In young rats, the subcutaneous median lethal dose is approximately 2000 mg/kg (approximately 14,000 times the maximum recommended daily inhalation dose for adults on a mg/m^2 basis and approximately 6400 times the maximum recommended daily inhalation dose for children on a mg/m^2 basis). The inhalation median lethal dose has not been determined in animals.

DOSAGE AND ADMINISTRATION

For treatment of acute episodes of bronchospasm or prevention of asthmatic symptoms, the usual dosage for adults and children 4 years of age and older is two inhalations repeated every 4 to 6 hours. More frequent administration or a larger number of inhalations is not recommended. In some patients, one inhalation every 4 hours may be sufficient. Each actuation of PROVENTIL® HFA Inhalation Aerosol delivers 108 mcg of albuterol sulfate (equivalent to 90 mcg of albuterol base) from the mouthpiece. It is recommended to prime the inhaler before using for the first time and in cases where the inhaler has not been used for more than 2 weeks by releasing four “test sprays” into the air, away from the face.

Exercise Induced Bronchospasm Prevention: The usual dosage for adults and children 4 years of age and older is two inhalations 15 to 30 minutes before exercise.

To maintain proper use of this product, it is important that the mouthpiece be washed and dried thoroughly at least once a week. The inhaler may cease to deliver medication if not properly cleaned and dried thoroughly (see PRECAUTIONS, Information for Patients section). Keeping the plastic mouthpiece clean is very important to prevent medication buildup and blockage. The inhaler may cease to deliver medication if not properly cleaned and air dried thoroughly. If the mouthpiece becomes blocked, washing the mouthpiece will remove the blockage.

If a previously effective dose regimen fails to provide the usual response, this may be a marker of destabilization of asthma and requires reevaluation of the patient and the treatment regimen, giving special consideration to the possible need for anti-inflammatory treatment, e.g., corticosteroids.

HOW SUPPLIED

PROVENTIL® HFA (albuterol sulfate) Inhalation Aerosol is supplied as a pressurized aluminum canister with a yellow plastic actuator and orange dust cap each in boxes of one. Each actuation delivers 120 mcg of albuterol sulfate from the valve and 108 mcg of albuterol sulfate from the mouthpiece (equivalent to 90 mcg of albuterol base). Canisters with a labeled net weight of 6.7 g contain 200 inhalations (NDC 0085-1132-01).

Rx only. Store between 15°-25°C (59°-77°F). Store the inhaler with the mouthpiece down. For best results, canister should be at room temperature before use.

SHAKE WELL BEFORE USING.

The yellow actuator supplied with PROVENTIL HFA Inhalation Aerosol should not be used with any other product canisters, and actuator from other products should not be used with a PROVENTIL HFA Inhalation Aerosol canister. The correct amount of medication in each canister cannot be assured after 200 actuations, even though the canister is not completely empty. The canister should be discarded when the labeled number of actuations have been used.

WARNING: Avoid spraying in eyes. Contents under pressure. Do not puncture or incinerate. Exposure to temperatures above 120°F may cause bursting. Keep out of reach of children.

PROVENTIL® HFA Inhalation Aerosol does not contain chlorofluorocarbons (CFCs) as the propellant.

Manufactured for:
Merck Sharp & Dohme Corp., a subsidiary of
MERCK & CO., INC.
Whitehouse Station, NJ 08889, USA

Developed and Manufactured by:
3M Health Care Limited
Loughborough UK

or

3M Drug Delivery Systems
Northridge, CA 91324, USA

Copyright © 1996, 2011, 2012
Merck Sharp & Dohme Corp., a subsidiary of Merck & Co., Inc. All rights reserved.
The trademarks depicted in this piece are owned by their respective companies.

653300
Rev. 07/18

Attention Health Care Professional:

Detach Patient's Instructions for Use from package insert and dispense with the product.

PROVENTIL® HFA

(albuterol sulfate)

Inhalation Aerosol

FOR ORAL INHALATION ONLY

Patient's Instructions for Use

Figure 1

Figure 2

Before using your PROVENTIL® HFA (albuterol sulfate) Inhalation Aerosol, read complete instructions carefully. Children should use PROVENTIL HFA Inhalation Aerosol under adult supervision, as instructed by the patient's doctor

Please note that indicates that this inhalation aerosol does not contain chlorofluorocarbons (CFCs) as the propellant.

1. SHAKE THE INHALER WELL immediately before each use. Then remove the cap from the mouthpiece (see Figure 1). Check mouthpiece for foreign objects prior to use. Make sure the canister is fully inserted into the actuator.
2. As with all aerosol medications, it is recommended to prime the inhaler before using for the first time and in cases where the inhaler has not been used for more than 2 weeks. Prime by releasing four “test sprays” into the air, away from your face.
3. BREATHE OUT FULLY THROUGH THE MOUTH, expelling as much air from your lungs as possible. Place the mouthpiece fully into the mouth, holding the inhaler in its upright position (see Figure 2) and closing the lips around it.
4. WHILE BREATHING IN DEEPLY AND SLOWLY THROUGH THE MOUTH, FULLY DEPRESS THE TOP OF THE METAL CANISTER with your index finger (see Figure 2).
5. HOLD YOUR BREATH AS LONG AS POSSIBLE, up to 10 seconds. Before breathing out, remove the inhaler from your mouth and release your finger from the canister.
6. If your physician has prescribed additional puffs, wait 1 minute, shake the inhaler again, and repeat steps 3 through 5. Replace the cap after use.
9. KEEPING THE PLASTIC MOUTHPIECE CLEAN IS EXTREMELY IMPORTANT TO PREVENT MEDICATION BUILDUP AND BLOCKAGE. THE MOUTHPIECE SHOULD BE WASHED, SHAKEN TO REMOVE EXCESS WATER, AND AIR DRIED THOROUGHLY AT LEAST ONCE A WEEK. INHALER MAY STOP SPRAYING IF NOT PROPERLY CLEANED. Routine cleaning instructions: Step 1. To clean, remove the canister and mouthpiece cap. Wash the mouthpiece through the top and bottom with warm running water for 30 seconds at least once a week (see Figure A). Never immerse the metal canister in water.
  Figure A
  Wash mouthpiece under warm running water.
  Figure B
  Allow mouthpiece to air dry, such as overnight.
  Figure C
  When blocked, little or no medicine comes out. Step 2. To dry, shake off excess water and let the mouthpiece air dry thoroughly, such as overnight (see Figure B). When the mouthpiece is dry, replace the canister and the mouthpiece cap. Blockage from medication buildup is more likely to occur if the mouthpiece is not allowed to air dry thoroughly. IF YOUR INHALER HAS BECOME BLOCKED (little or no medication coming out of the mouthpiece, see Figure C), wash the mouthpiece as described in Step 1 and air dry thoroughly as described in Step 2. IF YOU NEED TO USE YOUR INHALER BEFORE IT IS COMPLETELY DRY, SHAKE OFF EXCESS WATER, replace the canister, and test spray twice into the air, away from your face, to remove most of the water remaining in the mouthpiece. Then take your dose as prescribed. After such use, rewash and air dry thoroughly as described in Steps 1 and 2.
10. The correct amount of medication in each inhalation cannot be assured after 200 actuations, even though the canister is not completely empty. The canister should be discarded when the labeled number of actuations have been used. Before you reach the specific number of actuations, you should consult your physician to determine whether a refill is needed. Just as you should not take extra doses without consulting your physician, you also should not stop using PROVENTIL HFA Inhalation Aerosol without consulting your physician.

You may notice a slightly different taste or spray force than you are used to with PROVENTIL HFA Inhalation Aerosol, compared to other albuterol inhalation aerosol products.

DOSAGE:

Use only as directed by your physician.

WARNINGS:

The action of PROVENTIL® HFA Inhalation Aerosol should last up to 4 to 6 hours. PROVENTIL HFA Inhalation Aerosol should not be used more frequently than recommended. Do not increase the number of puffs or frequency of doses of PROVENTIL HFA Inhalation Aerosol without consulting your physician. If you find that treatment with PROVENTIL HFA Inhalation Aerosol becomes less effective for symptomatic relief, your symptoms become worse, and/or you need to use the product more frequently than usual, medical attention should be sought immediately. While you are taking PROVENTIL HFA Inhalation Aerosol, other inhaled drugs should be taken only as directed by your physician. If you are pregnant or nursing, contact your physician about the use of PROVENTIL HFA Inhalation Aerosol.

Common adverse effects of treatment with PROVENTIL HFA Inhalation Aerosol include palpitations, chest pain, rapid heart rate, tremor, or nervousness. Effective and safe use of PROVENTIL HFA Inhalation Aerosol includes an understanding of the way that it should be administered. Use PROVENTIL HFA Inhalation Aerosol only with the yellow actuator supplied with the product. The PROVENTIL HFA Inhalation Aerosol actuator should not be used with other aerosol medications.

For best results, use at room temperature. Avoid exposing product to extreme heat and cold.

Shake well before use.

Contents Under Pressure.

Do not puncture. Do not store near heat or open flame. Exposure to temperatures above 120°F may cause bursting. Never throw container into fire or incinerator. Store between 15° - 25°C (59° - 77°F). Store the inhaler with the mouthpiece down. Avoid spraying in eyes. Keep out of reach of children.

Further Information: Your PROVENTIL® HFA (albuterol sulfate) Inhalation Aerosol does not contain chlorofluorocarbons (CFCs) as the propellant. Instead, the inhaler contains a hydrofluoroalkane (HFA-134a) as the propellant.

Manufactured for:
Merck Sharp & Dohme Corp., a subsidiary of
MERCK & CO., INC.
Whitehouse Station, NJ 08889, USA

Developed and Manufactured by:
3M Health Care Limited
Loughborough UK
or
3M Drug Delivery Systems
Northridge, CA 91324, USA

Rev. 12/14; Copyright © 1996, 2011, 2012 Merck Sharp & Dohme Corp., a subsidiary of; Merck & Co., Inc.; All rights reserved. | 653300

Principal Display Panel – Trade Canister Label

NDC 0085-1132-01

PROVENTIL® HFA

(Albuterol Sulfate Inhalation Aerosol)

FOR ORAL INHALATION WITH

PROVENTIL® HFA ACTUATOR ONLY

Rx only

200 METERED INHALATIONS

NET CONTENTS 6.7g

Manuf. for Merck, Sharp &
Dohme Corp., a sub. of

MERCK & CO., INC

Whitehouse Station,

NJ 08889, USA

Principal Display Panel – Trade Carton Label

NDC 0085-1132-01

PROVENTIL® HFA

(Albuterol Sulfate Inhalation Aerosol)

FOR ORAL INHALATION WITH

PROVENTIL® HFA ACTUATOR ONLY

Rx only

200 METERED
INHALATIONS

NET CONTENTS 6.7g

CONTAINS NO

CHLOROFLUOROCARBONS [CFCs].